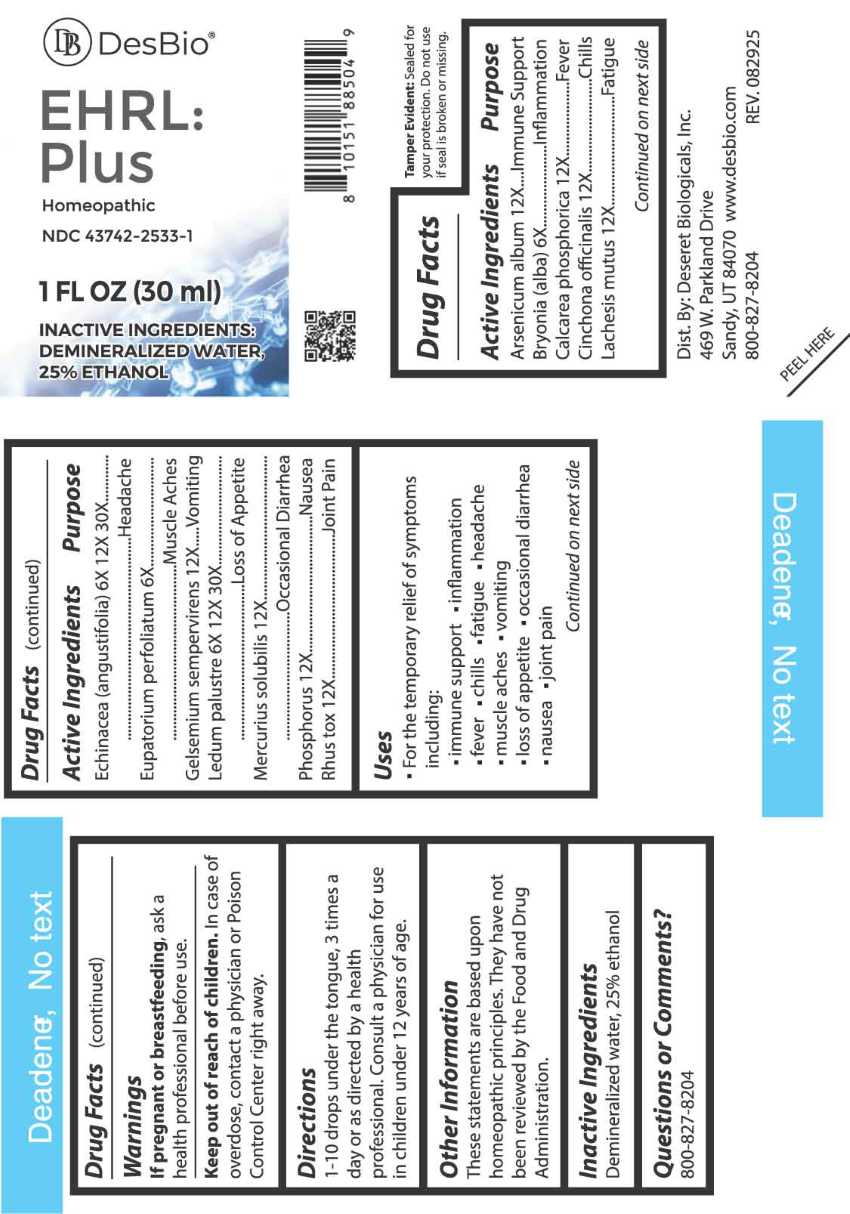 DRUG LABEL: EHRL Plus
NDC: 43742-2533 | Form: LIQUID
Manufacturer: Deseret Biologicals, Inc.
Category: homeopathic | Type: HUMAN OTC DRUG LABEL
Date: 20260102

ACTIVE INGREDIENTS: ARSENIC TRIOXIDE 12 [hp_X]/1 mL; BRYONIA ALBA ROOT 6 [hp_X]/1 mL; TRIBASIC CALCIUM PHOSPHATE 12 [hp_X]/1 mL; CINCHONA OFFICINALIS BARK 12 [hp_X]/1 mL; LACHESIS MUTA VENOM 12 [hp_X]/1 mL; ECHINACEA ANGUSTIFOLIA WHOLE 6 [hp_X]/1 mL; EUPATORIUM PERFOLIATUM FLOWERING TOP 6 [hp_X]/1 mL; GELSEMIUM SEMPERVIRENS ROOT 12 [hp_X]/1 mL; RHODODENDRON TOMENTOSUM LEAFY TWIG 6 [hp_X]/1 mL; MERCURIUS SOLUBILIS 12 [hp_X]/1 mL; PHOSPHORUS 12 [hp_X]/1 mL; TOXICODENDRON PUBESCENS LEAF 12 [hp_X]/1 mL
INACTIVE INGREDIENTS: WATER; ALCOHOL

DRUG FACTS:

ACTIVE INGREDIENTS:

Arsenicum Album 12X, Bryonia (Alba) 6X, Calcarea Phosphorica 12X, Cinchona Officinalis 12X, Lachesis Mutus 12X, Echinacea (Angustifolia) 6X, 12X, 30X, Eupatorium Perfoliatum 6X, Gelsemium Sempervirens 12X, Ledum Palustre 6X, 12X, 30X, Mercurius Solubilis 12X, Phosphorus 12X, Rhus Tox 12X.

PURPOSE:

Arsenicum Album – Immune Support, Bryonia (Alba) - Inflammation, Calcarea Phosphorica - Fever, Cinchona Officinalis - Chills, Lachesis Mutus - Fatigue, Echinacea (Angustifolia) - Headache, Eupatorium Perfoliatum – Muscle Aches, Gelsemium Sempervirens - Vomiting, Ledum Palustre – Loss of Appetite, Mercurius Solubilis – Occasional Diarrhea, Phosphorus - Nausea, Rhus Tox – Joint Pain

USES:

• For the temporary relief of symptoms including:

• immune support • inflammation • fever • chills • fatigue • headache • muscle aches

• vomiting • loss of appetite • occasional diarrhea • nausea • joint pain

These statements are based upon homeopathic principles. They have not been reviewed by the Food and Drug Administration.

WARNINGS:

If pregnant or breastfeeding, ask a health professional before use.

Keep out of reach of children. In case of overdose, contact a physician or Poison Control Center right away.

Tamper Evident: Sealed for your protection. Do not use if seal is broken or missing.

KEEP OUT OF REACH OF CHILDREN:

In case of overdose, contact a physician or Poison Control Center right away.

DIRECTIONS:

1-10 drops under the tongue, 3 times a day or as directed by a health professional. Consult a physician for use in children under 12 years of age.

INACTIVE INGREDIENTS:

Demineralized water, 25% ethanol

QUESTIONS:

Dist. By: Deseret Biologicals, Inc.

469 W. Parkland Drive

Sandy, UT 84070

www.desbio.com

800-827-8204

PACKAGE DISPLAY LABEL:

DesBio

EHRL:Plus

Homeopathic

NDC 43742-2533-1

1 FL OZ (30 ml)